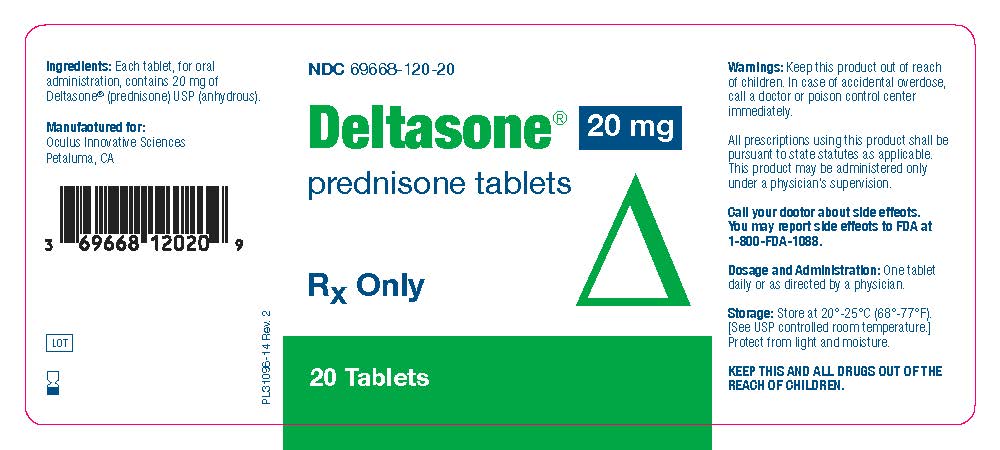 DRUG LABEL: Deltasone
NDC: 69668-120 | Form: TABLET
Manufacturer: Oculus Innovative Sciences
Category: prescription | Type: HUMAN PRESCRIPTION DRUG LABEL
Date: 20171107

ACTIVE INGREDIENTS: PREDNISONE 20 mg/20 mg

Deltasone 20mg prednisone tablets

Warnings

Warnings: Keep this product out of reach
of children. In case of accidental overdose,
call a doctor or poison control center
immediately.
All prescriptions using this product shall be
pursuant to state statutes as applicable.
This product may be administered only
under a physician’s supervision.
Call your doctor about side effects.
You may report side effects to FDA at
1-800-FDA-1088.